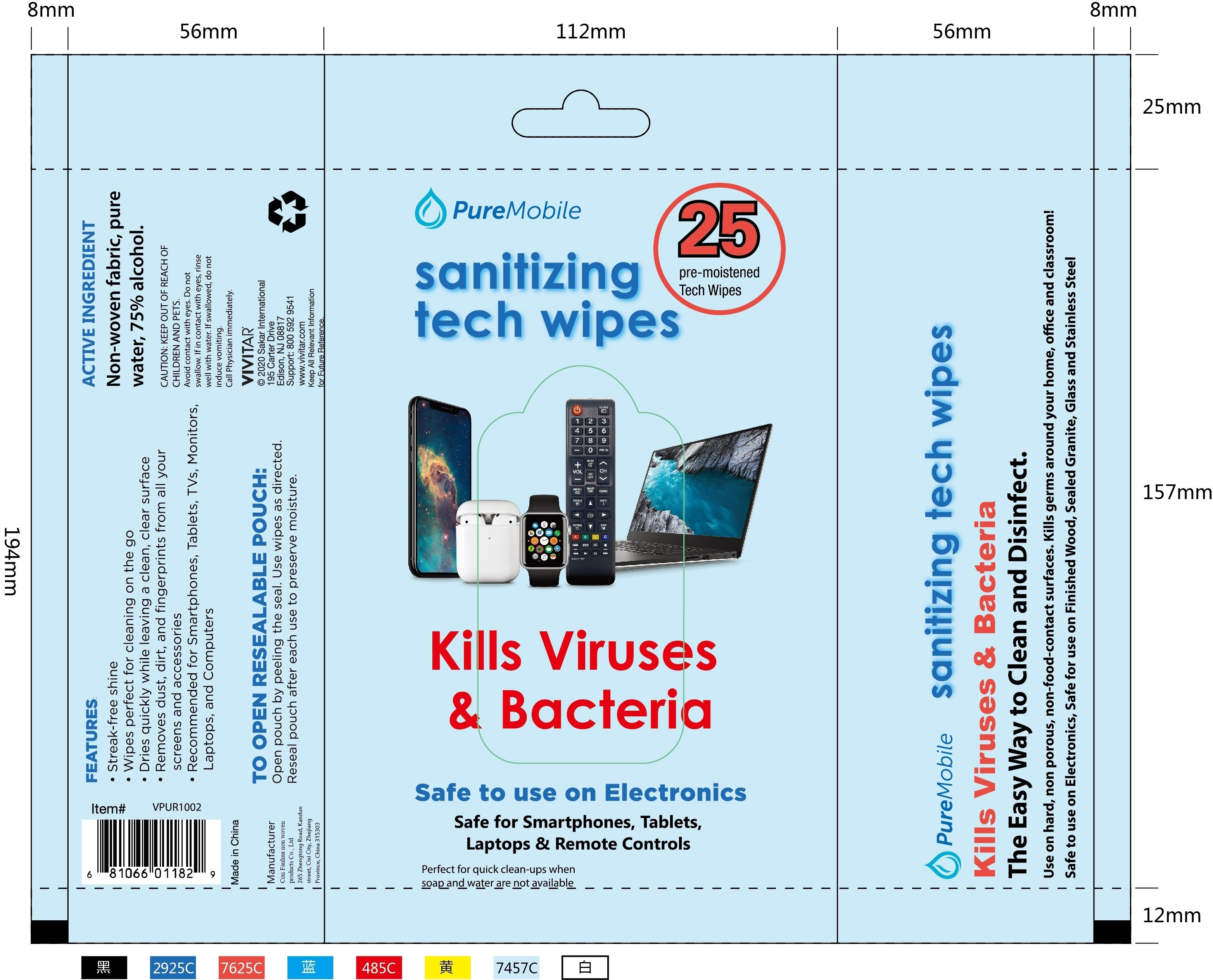 DRUG LABEL: sanitizing tech wipes
NDC: 54826-001 | Form: CLOTH
Manufacturer: Cixi Fanhua Non Woven Products Co., Ltd
Category: otc | Type: HUMAN OTC DRUG LABEL
Date: 20200521

ACTIVE INGREDIENTS: ALCOHOL 67.5 mL/25 1
INACTIVE INGREDIENTS: WATER

DOSAGE AND ADMINISTRATION

Store in a cool and dry place

INACTIVE INGREDIENT

Non-woven fabric,

pure water

Quaternary Ammonium Salt

INDICATIONS AND USAGE

Open pouch by peeling the seal. Use wipes as directed.Reseal pouch after each use to preserve moisture.

ACTIVE INGREDIENT

alcohol

keep out of reach of children

PURPOSE

Disinfection
Sterilization
No Rinseing

KEEP OUT OF REACH OF CHILDREN AND PETS.Avoid contact with eyes. Do not swallow. If in contact with eyes, rinse well with water. If swallowed, do not induce vomiting.Call Physician immediately.